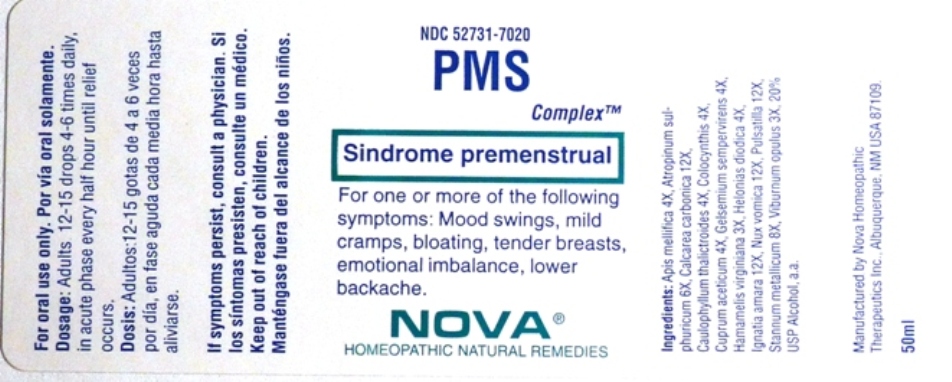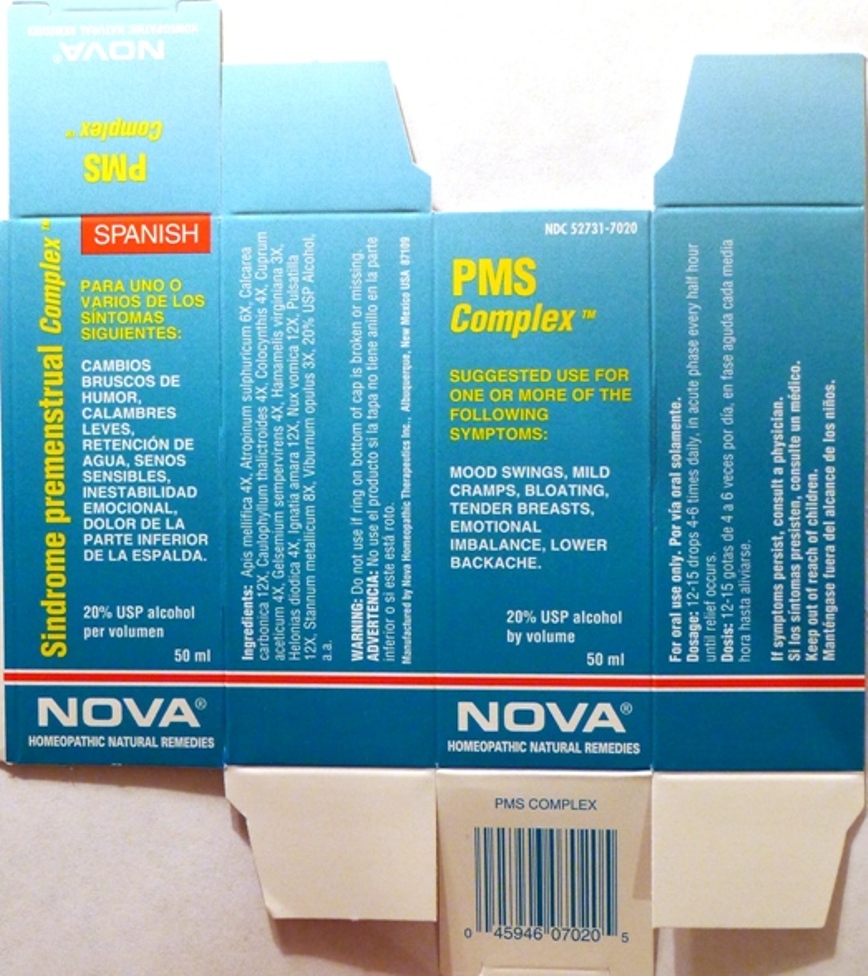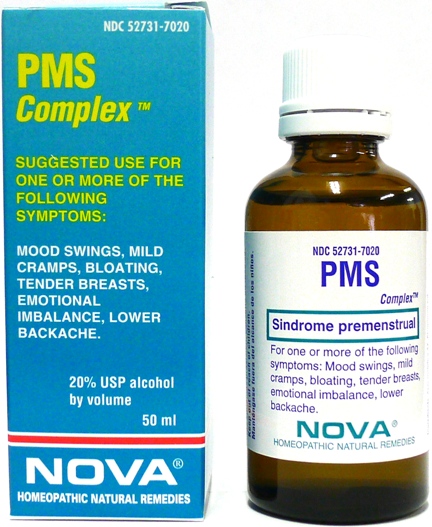 DRUG LABEL: PMS Complex
NDC: 52731-7020 | Form: LIQUID
Manufacturer: Nova Homeopathic Therapeutics, Inc.
Category: homeopathic | Type: HUMAN OTC DRUG LABEL
Date: 20110601

ACTIVE INGREDIENTS: APIS MELLIFERA 4 [hp_X]/1 mL; ATROPINE SULFATE 6 [hp_X]/1 mL; OYSTER SHELL CALCIUM CARBONATE, CRUDE 12 [hp_X]/1 mL; CAULOPHYLLUM THALICTROIDES ROOT 4 [hp_X]/1 mL; CITRULLUS COLOCYNTHIS FRUIT PULP 4 [hp_X]/1 mL; CUPRIC ACETATE 4 [hp_X]/1 mL; GELSEMIUM SEMPERVIRENS ROOT 4 [hp_X]/1 mL; HAMAMELIS VIRGINIANA ROOT BARK/STEM BARK 3 [hp_X]/1 mL; CHAMAELIRIUM LUTEUM ROOT 4 [hp_X]/1 mL; STRYCHNOS IGNATII SEED 12 [hp_X]/1 mL; STRYCHNOS NUX-VOMICA SEED 12 [hp_X]/1 mL; PULSATILLA VULGARIS 12 [hp_X]/1 mL; TIN 8 [hp_X]/1 mL; VIBURNUM OPULUS BARK 3 [hp_X]/1 mL
INACTIVE INGREDIENTS: ALCOHOL

PMS Complex

Purpose:

Suggested use for one or more of the following symptoms:

Mood swings, mild cramps, bloating, tender breasts, emotional imbalance, lower backache.

Usage and Dosage:

For oral use only.

DOSAGE AND ADMINISTRATION

Adults:
In Acute Phase:
12-15 drops, every half hour until relief occurs
When Relief Occurs:
12-15 drops, 4-6 times per day

Warnings:

Keep out of reach of children.

WARNINGS

If symptoms persist, consult a physician.
Do not use if ring on bottom of cap is broken or missing.

Active Ingredients:

Apis mellifica 4X, Atropinum sulphuricum 6X, Calcarea carbonica 12X, Caulophyllum thalictroides 4X, Colocynthis 4X, Cuprum aceticum 4X, Gelsemium sempervirens 4X, Hamamelis virginiana 3X, Helonias Dioica 4X, Ignatia amara 12X, Nux vomica 12X, Pulsatilla 12X, Stannum metalicum 8X, Viburnum opulus 3X

Inactive Ingredients:

Alcohol, 20% USP

QUESTIONS

Manufactured by Nova Homeopathic Therapeutics Inc., Albuquerque, New Mexico USA 87109
1-800-225-8094

PACKAGE LABEL

PMS Complex Product

PMS Complex Bottle Label

PMS Complex Box